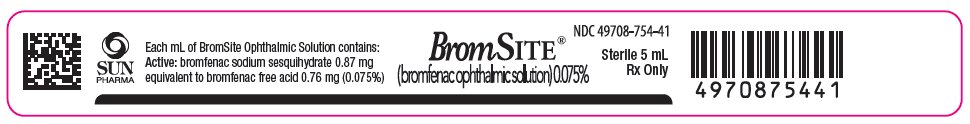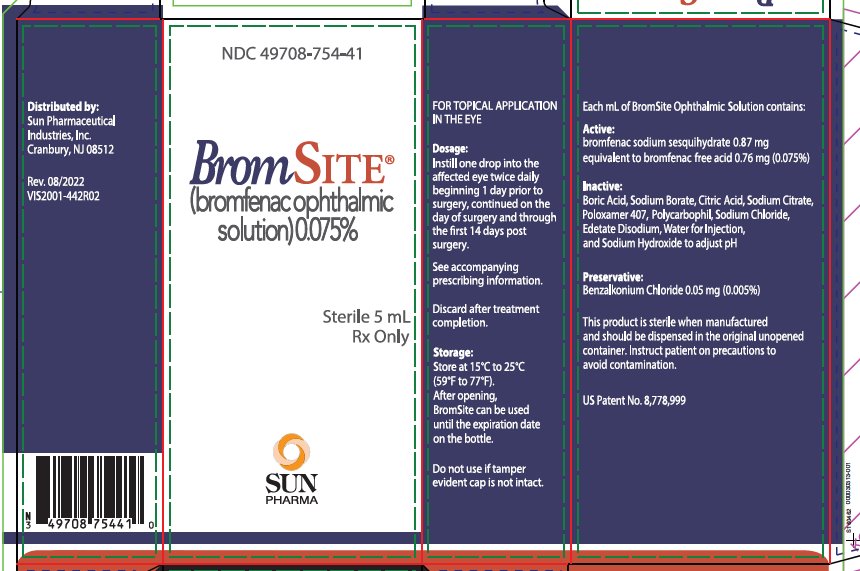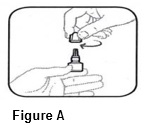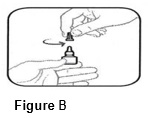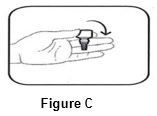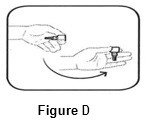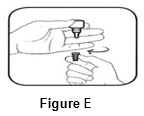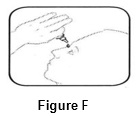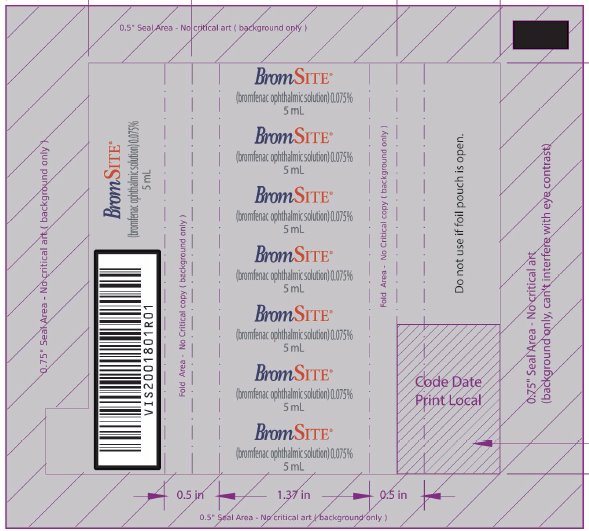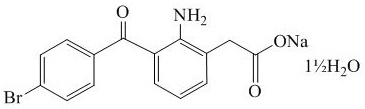 DRUG LABEL: BROMSITE

NDC: 49708-754 | Form: SOLUTION/ DROPS
Manufacturer: Sun Pharmaceutical Industries, Inc.
Category: prescription | Type: HUMAN PRESCRIPTION DRUG LABEL
Date: 20260108

ACTIVE INGREDIENTS: BROMFENAC SODIUM 0.76 mg/1 mL
INACTIVE INGREDIENTS: BORIC ACID; SODIUM BORATE; ANHYDROUS CITRIC ACID; TRISODIUM CITRATE DIHYDRATE; POLOXAMER 407; BENZALKONIUM CHLORIDE 0.05 mg/1 mL; POLYCARBOPHIL; SODIUM CHLORIDE; EDETATE DISODIUM; SODIUM HYDROXIDE; WATER

HIGHLIGHTS OF PRESCRIBING INFORMATION

These highlights do not include all the information needed to use BROMSITE®safely and effectively. See full prescribing information for BROMSITE.
BROMSITE (bromfenac ophthalmic solution) 0.075%, for topical ophthalmic use
Initial U.S. Approval: 1997

1 INDICATIONS AND USAGE

BromSite is a nonsteroidal anti-inflammatory drug (NSAID) indicated for the treatment of postoperative inflammation and prevention of ocular pain in patients undergoing cataract surgery. (1)

2 DOSAGE AND ADMINISTRATION

Instill one drop of BromSite to the affected eye twice daily (morning and evening) beginning 1 day prior to surgery, the day of surgery, and 14 days postsurgery. (2.1)

3 DOSAGE FORM AND STRENGTHS

Topical ophthalmic solution: bromfenac 0.075%. (3)

4 CONTRAINDICATIONS

None (4)

5 WARNINGS AND PRECAUTIONS

- Slow or Delayed Healing (5.1)
- Potential for Cross-Sensitivity (5.2)
- Increased Bleeding Time of Ocular Tissue (5.3)
- Keratitis and Corneal Effects (5.4)
- Contact Lens Wear (5.5)

6 ADVERSE REACTIONS

The most commonly reported adverse reactions in 1-8% of patients were: anterior chamber inflammation, headache, vitreous floaters, iritis, eye pain and ocular hypertension. (6.1)

To report SUSPECTED ADVERSE REACTIONS, contact Sun Pharmaceutical Industries, Inc. at 1-800-406-7984 (toll free), or FDA at 1-800-FDA-1088 or www.fda.gov/medwatch.

FULL PRESCRIBING INFORMATION

1 INDICATIONS AND USAGE

BromSite (bromfenac ophthalmic solution) 0.075% is indicated for the treatment of postoperative inflammation and prevention of ocular pain in patients undergoing cataract surgery.

2 DOSAGE AND ADMINISTRATION

2.1 Recommended Dosing

One drop of BromSite should be applied to the affected eye twice daily (morning and evening) 1 day prior to surgery, the day of surgery, and 14 days postsurgery.

2.2 Use with Other Topical Ophthalmic Medications

BromSite should be administered at least 5 minutes after instillation of other topical medications. BromSite may be administered in conjunction with other topical ophthalmic medications such as alpha-agonists, beta-blockers, carbonic anhydrase inhibitors, cycloplegics, and mydriatics.

3 DOSAGE FORM AND STRENGTHS

Topical ophthalmic solution: bromfenac 0.075%.

4 CONTRAINDICATIONS

None

5 WARNINGS AND PRECAUTIONS

5.1 Slow or Delayed Healing

All topical nonsteroidal anti-inflammatory drugs (NSAIDs), including BromSite (bromfenac ophthalmic solution) 0.075%, may slow or delay healing. Topical corticosteroids are also known to slow or delay healing. Concomitant use of topical NSAIDs and topical steroids may increase the potential for healing problems.

5.2 Potential for Cross-Sensitivity

There is the potential for cross-sensitivity to acetylsalicylic acid, phenylacetic acid derivatives, and other NSAIDs, including BromSite (bromfenac ophthalmic solution) 0.075%. Therefore, caution should be used when treating individuals who have previously exhibited sensitivities to these drugs.

5.3 Increased Bleeding Time of Ocular Tissue

With some NSAIDs, including BromSite (bromfenac ophthalmic solution) 0.075%, there exists the potential for increased bleeding time due to interference with platelet aggregation. There have been reports that ocularly applied NSAIDs may cause increased bleeding of ocular tissues (including hyphemas) in conjunction with ocular surgery.

It is recommended that BromSite be used with caution in patients with known bleeding tendencies or who are receiving other medications which may prolong bleeding time.

5.4 Keratitis and Corneal Reactions

Use of topical NSAIDs may result in keratitis. In some susceptible patients, continued use of topical NSAIDs may result in epithelial breakdown, corneal thinning, corneal erosion, corneal ulceration or corneal perforation. These events may be sight threatening. Patients with evidence of corneal epithelial breakdown should immediately discontinue use of topical NSAIDs, including BromSite (bromfenac ophthalmic solution) 0.075%, and should be closely monitored for corneal health.

Postmarketing experience with topical NSAIDs suggests that patients with complicated ocular surgeries, corneal denervation, corneal epithelial defects, diabetes mellitus, ocular surface diseases (e.g., dry eye syndrome), rheumatoid arthritis, or repeat ocular surgeries within a short period of time may be at increased risk for corneal adverse events which may become sight threatening. Topical NSAIDs should be used with caution in these patients.

Postmarketing experience with topical NSAIDs also suggests that use more than 24 hours prior to surgery or use beyond 14 days postsurgery may increase patient risk for the occurrence and severity of corneal adverse events.

5.5 Contact Lens Wear

BromSite should not be administered while wearing contact lenses. The preservative in BromSite, benzalkonium chloride, may be absorbed by soft contact lenses.

6 ADVERSE REACTIONS

The following serious adverse reactions are described elsewhere in the labeling:

- Slow or Delayed Healing [see Warnings and Precautions (5.1)]
- Potential for Cross-Sensitivity [see Warnings and Precautions (5.2)]
- Increased Bleeding Time of Ocular Tissue [see Warnings and Precautions (5.3)]
- Keratitis and Corneal Reactions[see Warnings and Precautions (5.4)]
- Contact Lens Wear [see Warnings and Precautions (5.5)]

6.1 Clinical Trials Experience

Because clinical trials are conducted under widely varying conditions, adverse reaction rates observed in the clinical trials of a drug cannot be directly compared to rates in the clinical trials of another drug and may not reflect the rates observed in clinical practice.
The most commonly reported adverse reactions in 1 to 8% of patients were: anterior chamber inflammation, headache, vitreous floaters, iritis, eye pain and ocular hypertension.

8 USE IN SPECIFIC POPULATIONS

8.1 Pregnancy

Risk Summary
There are no adequate and well-controlled studies in pregnant women to inform any drug associated risks. Treatment of pregnant rats and rabbits with oral bromfenac did not produce teratogenic effects at clinically relevant doses.
Clinical Considerations
Because of the known effects of prostaglandin biosynthesis-inhibiting drugs on the fetal cardiovascular system (closure of ductus arteriosus), the use of BromSite during late pregnancy should be avoided.

Data
Animal Data
Treatment of rats with bromfenac at oral doses up to 0.9 mg/kg/day (195 times a unilateral daily human ophthalmic dose on a mg/m^2basis, assuming 100% absorbed) and rabbits at oral doses up to 7.5 mg/kg/day (3243 times a unilateral daily dose on a mg/m^2basis) produced no structural teratogenicity in reproduction studies. However, embryo-fetal lethality, neonatal mortality and reduced postnatal growth were produced in rats at 0.9 mg/kg/day, and embryo-fetal lethality was produced in rabbits at 7.5 mg/kg/day. Because animal reproduction studies are not always predictive of human response, this drug should be used during pregnancy only if the potential benefit justifies the potential risk to the fetus.

8.2 Lactation

There are no data on the presence of bromfenac in human milk, the effects on the breastfed infant, or the effects on milk production; however, systemic exposure to bromfenac from ocular administration is low [see Clinical Pharmacology (12.3)]. The developmental and health benefits of breastfeeding should be considered along with the mother’s clinical need for bromfenac and any potential adverse effects on the breast-fed child from bromfenac or from the underlying maternal condition.

8.4 Pediatric Use

Safety and efficacy in pediatric patients below the age of 18 years have not been established.

8.5 Geriatric Use

There is no evidence that the efficacy or safety profiles for BromSite differ in patients 65 years of age and older compared to younger adult patients.

11 DESCRIPTION

BromSite (bromfenac ophthalmic solution) 0.075% is a sterile aqueous, topical NSAID, formulated in DuraSite®for ophthalmic use. The USAN name for bromfenac sodium sesquihydrate is bromfenac sodium. Bromfenac sodium is designated chemically as sodium [2-amino-3-(4-bromobenzoyl) phenyl] acetate sesquihydrate, with an empirical formula of C15H11BrNNaO3• 1½H2O. The structural formula for bromfenac sodium sesquihydrate is:

Bromfenac sodium is a bright orange to yellow powder. The molecular weight of bromfenac sodium sesquihydrate is 383.17. BromSite is a greenish-yellow to dark yellow viscous liquid with an osmolality of approximately 290 mOsmol/kg.
Active:Each mL contains bromfenac sodium sesquihydrate 0.87 mg, which is equivalent to bromfenac free acid 0.76 mg.
Preservative:benzalkonium chloride 0.005%
Inactives:boric acid, sodium borate, citric acid anhydrous, sodium citrate dihydrate, poloxamer 407, polycarbophil, sodium chloride, edetate disodium dihydrate, sodium hydroxide (to adjust pH to 8.3), and water for injection (USP).

12 CLINICAL PHARMACOLOGY

12.1 Mechanism of Action

Bromfenac is a nonsteroidal anti-inflammatory drug (NSAID) that has anti-inflammatory activity. The mechanism of its action is thought to be due to its ability to block prostaglandin synthesis by inhibiting cyclooxygenase 1 and 2. Prostaglandins have been shown in many animal models to be mediators of certain kinds of intraocular inflammation. In studies performed in animal eyes, prostaglandins have been shown to produce disruption of the blood-aqueous humor barrier, vasodilation, increased vascular permeability, leukocytosis, and increased intraocular pressure.

12.3 Pharmacokinetics

Following bilateral topical ocular twice-daily dosing of Bromfenac 0.075% ophthalmic solution, the plasma concentrations of bromfenac ranged from below the limit of quantification (LOQ = 0.20 ng/mL) to 2.42 ng/mL at 30 to 60 minutes post-dose.

13 NONCLINICAL TOXICOLOGY

13.1 Carcinogenesis, Mutagenesis and Impairment of Fertility

Long-term carcinogenicity studies in rats and mice given oral doses of bromfenac up to 0.6 mg/kg/day (129 times a unilateral daily dose assuming 100% absorbed, on a mg/m^2basis) and 5 mg/kg/day (540 times a unilateral daily dose on a mg/m^2basis), respectively revealed no significant increases in tumor incidence.
Bromfenac did not show mutagenic potential in various mutagenicity studies, including the bacterial reverse mutation, chromosomal aberration, and micronucleus tests.
Bromfenac did not impair fertility when administered orally to male and female rats at doses up to 0.9 mg/kg/day and 0.3 mg/kg/day, respectively (195 and 65 times a unilateral daily dose, respectively, on a mg/m^2basis).

14 CLINICAL STUDIES

14.1 Ocular Inflammation and Pain

Clinical efficacy was evaluated in 2 multi-centered, randomized, double-masked, parallel group, placebo-controlled US trials in which subjects requiring cataract surgery were assigned to receive BromSite or vehicle. Patients undergoing cataract surgery self-administered BromSite or vehicle twice daily, beginning 1 day prior to surgery, continuing the day of surgery and for 14 days after surgery. Clearance of ocular inflammation was assessed on Days 1, 8, 15, and 29 using slit lamp biomicroscopy. The primary efficacy endpoint was the proportion of subjects with anterior chamber cell (ACC) grade 0 at Day 15. The secondary efficacy endpoint was the proportion of subjects who were pain free after cataract surgery as assessed using a Visual Analog Scale.

Proportion of Subjects with Cleared Ocular Inflammation, ACC Grade 0
 | Visit | BromSite | Vehicle | Treatment Difference (95% CI)
Study 1 | Day 8 | 54/168 (32.1%) | 7/85 (8.2%) | 23.9% (14.7%, 33.1%)
 | Day 15 | 96/168 (57.1%) | 16/85 (18.8%) | 38.3% (27.1%, 49.5%)
Study 2 | Day 8 | 40/168 (23.8%) | 8/85 (9.4%) | 1 4.4% (5.5%, 23.3%)
 | Day 15 | 64/168 (38.1%) | 19/85 (22.4%) | 1 5.7% (4.2%, 27.3%)
Proportion of Subjects who were Pain Free
Study 1 | Day 1 | 129/168 (76.8%) | 41/85 (48.2%) | 28.6% (16.2%, 40.9%)
Study 2 | Day 1 | 138/168 (82.1%) | 53/85 (62.4%) | 19.8% (8.0%, 31.6%)

16 HOW SUPPLIED/STORAGE AND HANDLING

BromSite (bromfenac ophthalmic solution) 0.075% is supplied in white opaque low density polyethylene (LDPE) plastic bottles and translucent dropper tips, and gray high density polyethylene (HDPE) eyedropper caps. A white tamper evident overcap is provided. Each bottle is provided in a sealed foil laminated pouch.
5 mL in a 7.5 mL bottle
(NDC No. 49708-754-41)
STORAGE
Store at 15°C to 25°C (59°F to 77°F). After opening, BromSite can be used until the expiration date on the bottle. Discard after treatment completion.

17 PATIENT COUNSELING INFORMATION

Advise the patient to read the FDA-approved patient labeling (Instructions for Use).
Slow or Delayed Healing
Advise patients of the possibility that slow or delayed healing may occur while using NSAIDs.
Concomitant Topical Ocular Therapy
If more than one topical ophthalmic medication is being used, advise patients to administer BromSite at least 5 minutes after instillation of other topical medications.
Concomitant Use of Contact Lenses
Advise patients not to wear contact lenses during administration of BromSite. The preservative in this product, benzalkonium chloride, may be absorbed by soft contact lenses.

Sterility of Dropper Tip/Product Use
Advise patients to replace the bottle cap after use and do not touch the dropper tip to any surface as this may contaminate the contents.
Advise patients to thoroughly wash hands prior to using BromSite.

Distributed by:
Sun Pharmaceutical Industries, Inc.
Cranbury, NJ 08512

US Patent No. 8,778,999

BromSite and DuraSite are registered trademarks of Sun Pharmaceutical Industries Limited

© 2022 Sun Pharmaceutical Industries, Inc. All rights reserved.

Rev: MM/YYYY

VISX001-642R02

INSTRUCTIONS FOR USE

BromSite®[BRŏM- sahyt]
(bromfenac ophthalmic solution) 0.075%

Read this Instructions for Use before you start using BromSite and each time you get a refill. There may be new information. This leaflet does not take the place of talking to your healthcare provider about your medical condition or treatment.

Information about BromSite:

• Do notlet the BromSite applicator tip touch your eye, fingers, or any other surfaces.
• If you are using BromSite with other eye (ophthalmic) medicines, you should wait at least 5 minutesafter using the other medicine to give your BromSite dose.
• You should not wear contact lenses while using BromSite.
• Put the gray cap back on the BromSite after each use.

Before you use BromSite for the first time:

• Tear open the foil pouch using the perforated notch and remove the BromSite bottle. Throw away the foil pouch.
• Remove the white cap by turning it in the clockwise direction (See FIGURE A). Throw away the white cap.

• Hold the bottle upright. Remove the gray cap by turning it in the counterclockwise direction (See FIGURE B).

• Replace the gray cap on the bottle and close tightly.

Follow Steps 1 to 5 each time you use BromSite.

Step 1.Wash your hands well.

Step 2.Turn the closed bottle upside down (See FIGURE C).

Step 3.Flick bottle firmly 1 time before each use to move the medicine into the tip of the bottle (See FIGURE D).

Step 4.Keep the bottle upside down and remove the gray cap by turning it in the clockwise direction (See FIGURE E).

Step 5.Tilt your head back. Gently squeeze the bottle to place 1 drop into the affected eye (See FIGURE F). Replace the gray cap on the bottle and close tightly.

How do I store BromSite?

• Store at 15°C to 25°C (59°F to 77°F). After opening, BromSite can be used until the expiration date on the bottle.
• Throw away the BromSite bottle after your treatment is finished.

This Instructions for Use has been approved by the U.S. Food and Drug Administration.

Distributed by:
Sun Pharmaceutical Industries, Inc.
Cranbury, NJ 08512
US Patent No. 8,778,999

BromSite and DuraSite are registered trademarks of Sun Pharmaceutical Industries Limited
© 2022 Sun Pharmaceutical Industries, Inc. All rights reserved

Rev.: 03/2023
VISX001650R01